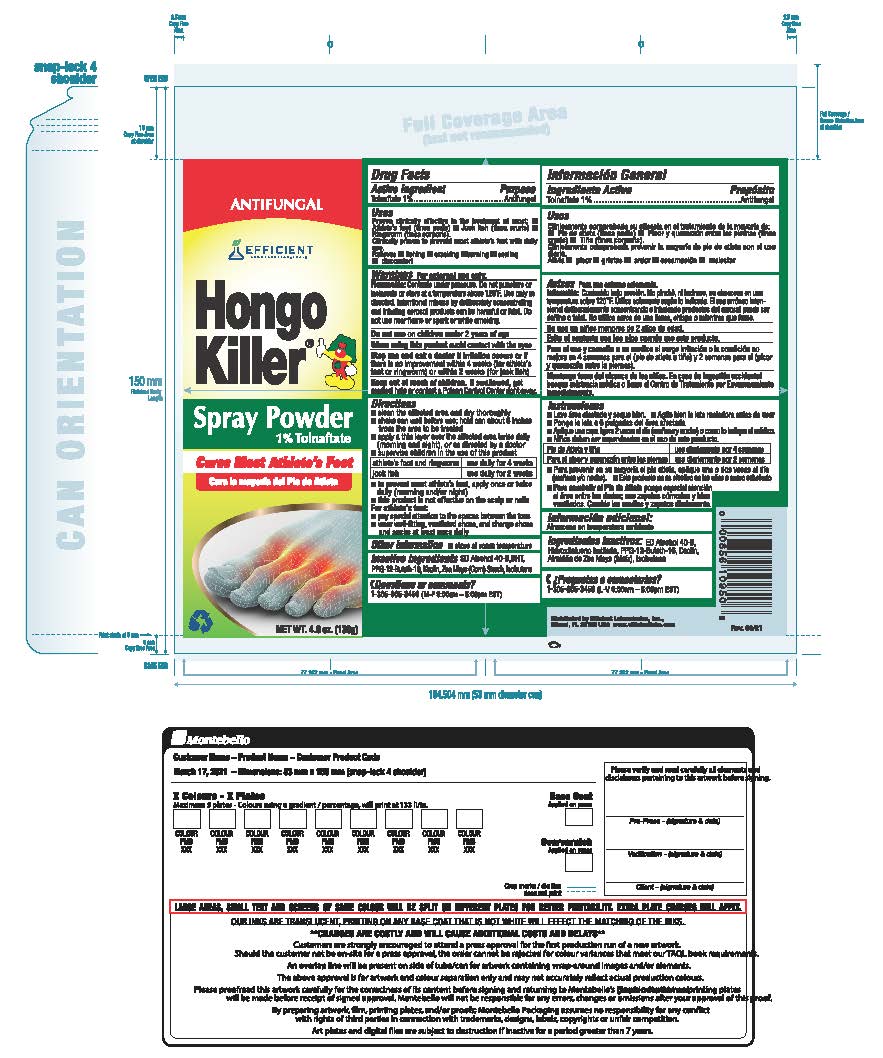 DRUG LABEL: Hongo Killer
NDC: 58593-285 | Form: AEROSOL, POWDER
Manufacturer: Efficient Laboratories Inc
Category: otc | Type: HUMAN OTC DRUG LABEL
Date: 20251014

ACTIVE INGREDIENTS: TOLNAFTATE 0.1 g/10 g
INACTIVE INGREDIENTS: ALCOHOL; STARCH, CORN; BUTYLATED HYDROXYTOLUENE; ISOBUTANE; KAOLIN; PPG-12-BUTETH-16

Drug Facts

Active Ingredients: Purpose

Tolnaftate 1% W/W........................ Antifungal

Purpose: Antifungal

Uses

Proven clinically effective in the treatment of most:

- athlete's foot (tinea pedis)
- jock itch (tinea cruris)
- ringworm (tinea corporis)

Clinically proven to prevent most athlete's foot with dauly use

Relieves

- itching
- cracking
- burning
- scaling
- discomfort

Warnings

For external use only

Flammable:Contents under pressure. Do not puncture or incinerate or store at a temperature above 120 degrees F. Use only as directed. intentional misuse by deliberately concentrating and inhaling aerosol products can be harmful or fatal. Do not use near flame or spark or while smoking.

Do not use on children under 2 years of age

When using this product avoid contact with eyes
Stop use and ask a doctor if irritation occurs or if there is no improvement within 4 weeks (for athlete's foot or ringworm) or within 2 weeks (for jock itch)

Keep out of reach of children. If swallowed, get medical help or contact a Poison Control Center right away.

Directions

- clean the affected area and dry thoroughly
- shake can well before use: Hold can about 6 inches from the area to be treated.
- apply a thin layer over the affected area twice daily (morning and night), or as directed by a doctor
- supervise children in the use of this product

Athlete's Foot and Ringworm - use daily for 4 weeks

Jock Itch - use daily for 2 weeks

- to prevent most athlete's foot, apply once or twice daily (morning and/or night)
- this product is not effective on the scalp or nails

For athlete's foot:

- pay special attention to the spaces between the toes
- wear well-fitting, ventilated shoes, and change shoes and socks at least once a day

Questions or comments?

Please Call 305-805-3456 (M-F 9:00-5:00 pm EST)

INACTIVE INGREDIENT

Inactive ingredients Alcohol SD-40-B (14% w/w), BHT, PPG-12-Buteth-16, Kaolin, Zea Mays (Corn) Starch, Isobutane